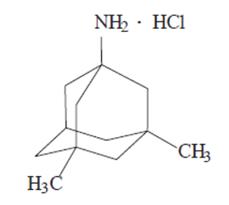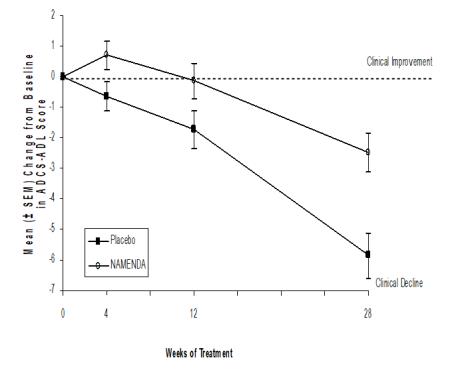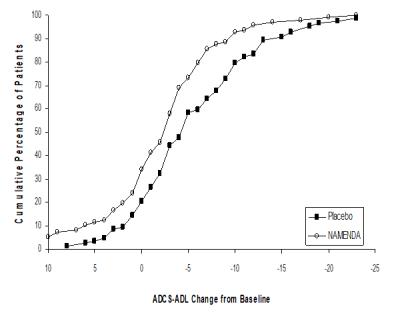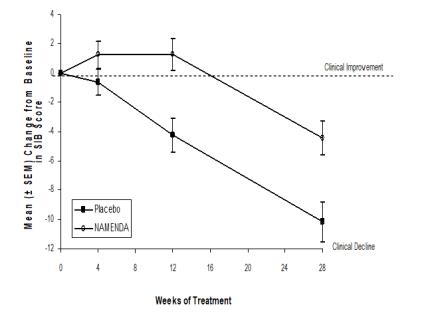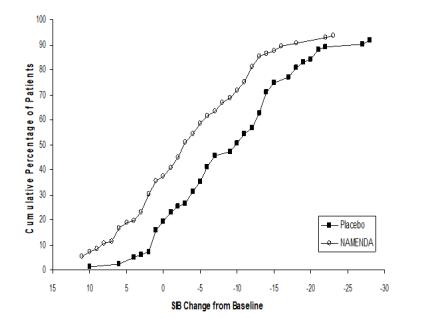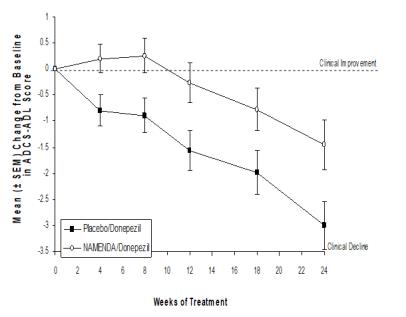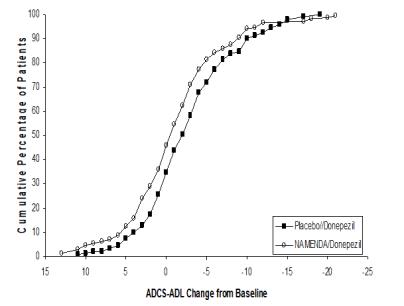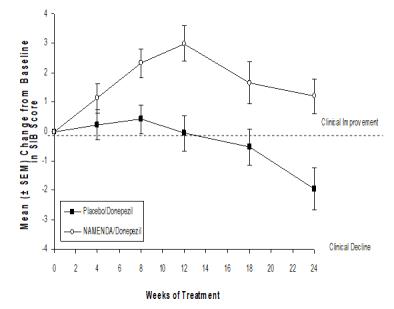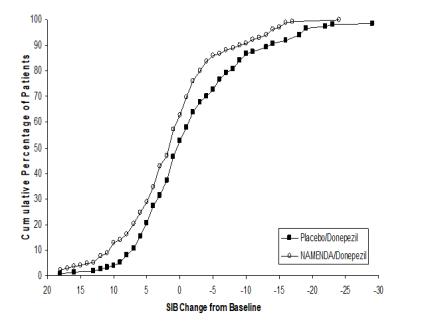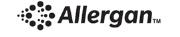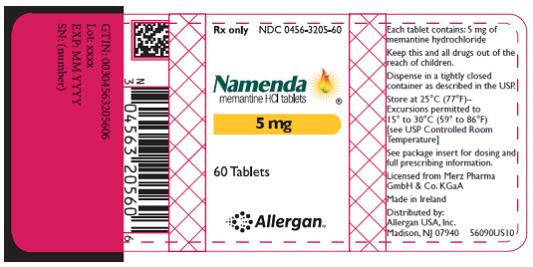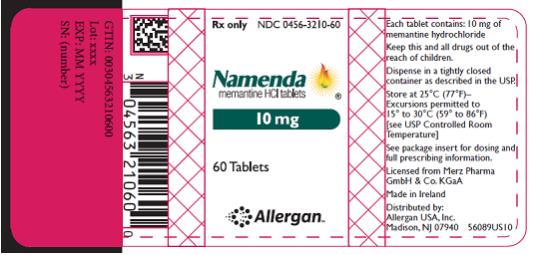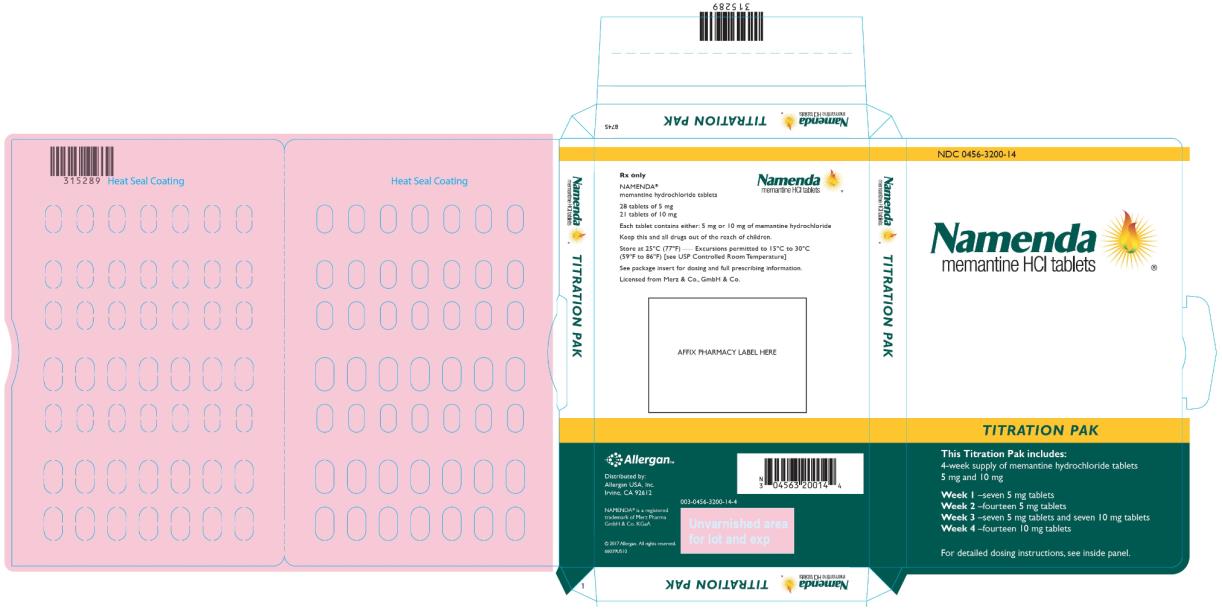 DRUG LABEL: Namenda
NDC: 0456-3205 | Form: TABLET
Manufacturer: Allergan, Inc.
Category: prescription | Type: HUMAN PRESCRIPTION DRUG LABEL
Date: 20181101

ACTIVE INGREDIENTS: MEMANTINE HYDROCHLORIDE 5 mg/1 1
INACTIVE INGREDIENTS: cellulose, microcrystalline; silicon dioxide; talc; croscarmellose sodium; magnesium stearate; HYPROMELLOSE, UNSPECIFIED; titanium dioxide; polyethylene glycol 400; FD&C YELLOW NO. 6; FD&C blue No. 2

HIGHLIGHTS OF PRESCRIBING INFORMATION

These highlights do not include all the information needed to use NAMENDA safely and effectively. See full prescribing information for NAMENDA.
NAMENDA® (memantine hydrochloride) tablets, for oral use
Initial U.S. Approval: 2003

1 INDICATIONS AND USAGE

NAMENDA is a N-methyl-D-aspartate (NMDA) receptor antagonist indicated for the treatment of moderate to severe dementia of the Alzheimer’s type. (1)

2 DOSAGE AND ADMINISTRATION

- May be taken with or without food. (2)
- Initial dose is 5 mg once daily. Increase dose in 5 mg increments to a maintenance dose of 10 mg twice daily. A minimum of 1 week of treatment with the previous dose should be observed before increasing the dose. (2)
- Severe renal impairment: recommended dose is 5 mg twice daily. (2)

3 DOSAGE FORMS AND STRENGTHS

Tablets: 5 mg and 10 mg (3)

4 CONTRAINDICATIONS

- NAMENDA is contraindicated in patients with known hypersensitivity to memantine hydrochloride or to any excipients used in the formulation. (4)

5 WARNINGS AND PRECAUTIONS

- Conditions that raise urine pH may decrease the urinary elimination of memantine, resulting in increased plasma levels of memantine. (5.1, 7.1)

6 ADVERSE REACTIONS

Most common adverse reactions (≥ 5% and greater than placebo) are dizziness, headache, confusion and constipation. (6.1)

To report SUSPECTED ADVERSE REACTIONS, contact Allergan at 1-800-678-1605 or FDA at 1-800-FDA-1088 or www.fda.gov/medwatch.

FULL PRESCRIBING INFORMATION

1 INDICATIONS AND USAGE

NAMENDA (memantine hydrochloride) is indicated for the treatment of moderate to severe dementia of the Alzheimer’s type.

2 DOSAGE AND ADMINISTRATION

The recommended starting dose of NAMENDA is 5 mg once daily. The dose should be increased in 5 mg increments to 10 mg/day (5 mg twice daily), 15 mg/day (5 mg and 10 mg as separate doses), and 20 mg/day (10 mg twice daily). The minimum recommended interval between dose increases is one week. The dosage shown to be effective in controlled clinical trials is 20 mg/day.

NAMENDA can be taken with or without food. If a patient misses a single dose of NAMENDA, that patient should not double up on the next dose. The next dose should be taken as scheduled.

If a patient fails to take NAMENDA for several days, dosing may need to be resumed at lower doses and retitrated as described above.

Specific Populations

Renal Impairment

A target dose of 5 mg twice daily is recommended in patients with severe renal impairment (creatinine clearance of 5 – 29 mL/min based on the Cockcroft-Gault equation).

Hepatic Impairment

NAMENDA should be administered with caution to patients with severe hepatic impairment [see Clinical Pharmacology (12.3)].

3 DOSAGE FORMS AND STRENGTHS

NAMENDA 5 mg Tablet: capsule-shaped, film-coated tablets are tan, with the strength “5” debossed on one side and “FL” on the other side.

NAMENDA 10 mg Tablet: capsule-shaped, film-coated tablets are gray, with the strength “10” debossed on one side and “FL” on the other side.

4 CONTRAINDICATIONS

NAMENDA (memantine hydrochloride) is contraindicated in patients with known hypersensitivity to memantine hydrochloride or to any excipients used in the formulation.

5 WARNINGS AND PRECAUTIONS

5.1 Genitourinary Conditions

Conditions that raise urine pH may decrease the urinary elimination of memantine resulting in increased plasma levels of memantine [see Drug Interactions (7.1)].

6 ADVERSE REACTIONS

6.1 Clinical Trials Experience

NAMENDA was evaluated in eight double-blind placebo-controlled trials involving a total of 1862 dementia (Alzheimer’s disease, vascular dementia) patients (940 patients treated with NAMENDA and 922 patients treated with placebo) for a treatment period up to 28 weeks.

Because clinical trials are conducted under widely varying conditions, adverse reaction rates observed in the clinical trials of a drug cannot be directly compared to rates in the clinical trials of another drug and may not reflect the rates observed in clinical practice.

Adverse Events Leading to Discontinuation

In placebo-controlled trials in which dementia patients received doses of NAMENDA up to 20 mg/day, the likelihood of discontinuation because of an adverse reaction was the same in the NAMENDA group (10.1%) as in the placebo group (11.5%). No individual adverse reaction was associated with the discontinuation of treatment in 1% or more of NAMENDA-treated patients and at a rate greater than placebo.

Most Common Adverse Reactions

In double-blind placebo-controlled trials involving dementia patients, the most common adverse reactions (incidence ≥ 5% and higher than placebo) in patients treated with NAMENDA were dizziness, headache, confusion and constipation. Table 1 lists all adverse reactions that occurred in at least 2% of patients treated with NAMENDA and at an incidence greater than placebo.

Table 1: Adverse Reactions Reported in Controlled Clinical Trials in at Least 2% of Patients Receiving NAMENDA and at a Higher Frequency than Placebo-Treated Patients
Adverse Reaction | Placebo (N=922) % | NAMENDA (N=940) %
Body as a Whole
Fatigue | 1 | 2
Pain | 1 | 3
Cardiovascular System
Hypertension | 2 | 4
Central and Peripheral Nervous System
Dizziness | 5 | 7
Headache | 3 | 6
Gastrointestinal System
Constipation | 3 | 5
Vomiting | 2 | 3
Musculoskeletal System
Back pain | 2 | 3
Psychiatric Disorders
Confusion | 5 | 6
Somnolence | 2 | 3
Hallucination | 2 | 3
Respiratory System
Coughing | 3 | 4
Dyspnea | 1 | 2

The overall profile of adverse reactions and the incidence rates for individual adverse reactions in the subpopulation of patients with moderate to severe Alzheimer’s disease were not different from the profile and incidence rates described above for the overall dementia population.

Seizures

NAMENDA has not been systematically evaluated in patients with a seizure disorder. In clinical trials of NAMENDA, seizures occurred in 0.2% of patients treated with NAMENDA and 0.5% of patients treated with placebo.

6.2 Postmarketing Experience

The following adverse reactions have been identified during post-approval use of memantine.

Because these reactions are reported voluntarily from a population of uncertain size, it is not always possible to reliably estimate their frequency or establish a causal relationship to drug exposure. These reactions include:

Blood and Lymphatic System Disorders - agranulocytosis, leukopenia (including neutropenia), pancytopenia, thrombocytopenia, thrombotic thrombocytopenic purpura.

Cardiac Disorders - cardiac failure congestive.

Gastrointestinal Disorders - pancreatitis.

Hepatobiliary Disorders - hepatitis.

Psychiatric Disorders - suicidal ideation.

Renal and Urinary Disorders - acute renal failure (including increased creatinine and renal insufficiency).

Skin Disorders - Stevens Johnson syndrome.

7 DRUG INTERACTIONS

7.1 Drugs that Make Urine Alkaline

The clearance of memantine was reduced by about 80% under alkaline urine conditions at pH 8. Therefore, alterations of urine pH towards the alkaline condition may lead to an accumulation of the drug with a possible increase in adverse effects. Urine pH is altered by diet, drugs (e.g. carbonic anhydrase inhibitors, sodium bicarbonate) and clinical state of the patient (e.g. renal tubular acidosis or severe infections of the urinary tract). Hence, memantine should be used with caution under these conditions.

7.2 Use with Other N-methyl-D-aspartate (NMDA) Antagonists

The combined use of NAMENDA with other NMDA antagonists (amantadine, ketamine, and dextromethorphan) has not been systematically evaluated and such use should be approached with caution.

8 USE IN SPECIFIC POPULATIONS

8.1 Pregnancy

Risk Summary

There are no adequate data on the developmental risk associated with the use of NAMENDA in pregnant women.

Adverse developmental effects (decreased body weight, and skeletal ossification) were observed in the offspring of rats administered memantine during pregnancy at doses associated with minimal maternal toxicity. These doses are higher than those used in humans at the maximum recommended daily dose of NAMENDA [see Data].

In the U.S. general population, the estimated background risk of major birth defects and miscarriage in clinically recognized pregnancies is 2-4% and 15-20%, respectively. The background risk of major birth defects and miscarriage for the indicated population is unknown.

Data

Animal Data

Oral administration of memantine (0, 2, 6, or 18 mg/kg/day) to rats during the period of organogenesis resulted in decreased skeletal ossification in fetuses at the highest dose tested. The higher no-effect dose for adverse developmental effects (6 mg/kg) is 3 times the maximum recommended human daily dose (MRHD) of NAMENDA (20 mg) on a body surface area (mg/m^2) basis.

Oral administration of memantine to rabbits (0, 3, 10, or 30 mg/kg/day) during the period of organogenesis resulted in no adverse developmental effects. The highest dose tested is approximately 30 times the MRHD of NAMENDA on a mg/m^2 basis.

In rats, memantine (0, 2, 6, or 18 mg/kg/day) was administered orally prior to and throughout mating and, in females, through the period of organogenesis or continuing throughout lactation to weaning. Decreased skeletal ossification in fetuses and decreased body weight in pups were observed at the highest dose tested. The higher no-effect dose for adverse developmental effects (6 mg/kg/day) is 3 times the MRHD of NAMENDA on a mg/m^2 basis.

Oral administration of memantine (0, 2, 6, or 18 mg/kg/day) to rats from late gestation throughout lactation to weaning, resulted in decreased pup weights at the highest dose tested. The higher no-effect dose (6 mg/kg/day) is approximately 3 times the MRHD of NAMENDA on a mg/m^2 basis.

8.2 Lactation

Risk Summary

There are no data on the presence of memantine in human milk, the effects on the breastfed infant, or the effects of NAMENDA on milk production.

The developmental and health benefits of breastfeeding should be considered along with the mother’s clinical need for NAMENDA and any potential adverse effects on the breastfed infant from NAMENDA or from the underlying maternal condition.

8.4 Pediatric Use

Safety and effectiveness in pediatric patients have not been established.

Memantine failed to demonstrate efficacy in two 12-week controlled clinical studies of 578 pediatric patients aged 6-12 years with autism spectrum disorders (ASD), including autism, Asperger’s disorder and Pervasive Development Disorder - Not Otherwise Specified (PDD-NOS). Memantine has not been studied in pediatric patients under 6 years of age or over 12 years of age. Memantine treatment was initiated at 3 mg/day and the dose was escalated to the target dose (weight-based) by week 6. Oral doses of memantine 3, 6, 9, or 15 mg extended-release capsules were administered once daily to patients with weights < 20 kg, 20-39 kg, 40-59 kg and ≥ 60 kg, respectively.

In a randomized, 12-week double-blind, placebo-controlled parallel study (Study A) in patients with autism, there was no statistically significant difference in the Social Responsiveness Scale (SRS) total raw score between patients randomized to memantine (n=54) and those randomized to placebo (n=53). In a 12-week responder-enriched randomized withdrawal study (Study B) in 471 patients with ASD, there was no statistically significant difference in the loss of therapeutic response rates between patients randomized to remain on full-dose memantine (n=153) and those randomized to switch to placebo (n=158).

The overall risk profile of memantine in pediatric patients was generally consistent with the known risk profile in adults [see Adverse Reactions (6.1)].

In Study A, the adverse reactions in the memantine group (n=56) that were reported in at least 5% of patients and at least twice the frequency of the placebo group (N=58) are listed in Table 2:

Table 2: Study A Commonly Reported Adverse Reactions with a Frequency ≥ 5% and Twice That of Placebo
Adverse Reaction | Memantine N=56 | Placebo N=58
Cough | 8.9% | 3.4%
Influenza | 7.1% | 3.4%
Rhinorrhea | 5.4% | 0%
Agitation | 5.4% | 1.7%
Discontinuations due to Adverse Reactionsa
Aggression | 3.6% | 1.7%
Irritability | 1.8% | 3.4%
a Reported adverse reactions leading to discontinuation in more than one patient in
either treatment group.

The adverse reactions that were reported in at least 5% of patients in the 12-48 week open-label study to identify responders to enroll in Study B are listed in Table 3:

Table 3: 12-48 Week Open Label Lead-In study to Study B Commonly Reported Adverse Reactions with a Frequency ≥ 5%
Adverse Reaction | Memantine N=903
Headache | 8.0%
Nasopharyngitis | 6.3%
Pyrexia | 5.8%
Irritability | 5.4%
Discontinuations due to Adverse Reactionsa
Irritability | 1.2%
Aggression | 1.0%
a At least 1% incidence of adverse reactions leading to premature discontinuation.

In the randomized withdrawal study (Study B), the adverse reaction in patients randomized to placebo (n=160) and reported in at least 5% of patients and at twice the frequency of the full-dose memantine treatment group (n=157) was irritability (5.0% vs 2.5%).

Juvenile Animal Study

In a study in which memantine (0, 15, 30 or 45 mg/kg/day) was orally administered to rats during the juvenile period of development (postnatal days [PND] 14 through 70), delays in sexual maturation were noted in males and females at all but the lowest dose tested, and body weight was reduced at the high dose. In rats orally administered memantine as a single dose (PND 14) or three daily doses (PND 14-16), neuronal lesions were observed in several areas of the brain at all but the lowest dose tested. Adverse neurobehavioral effects (decreased auditory startle habituation) were observed at the high dose. The no-effect dose for developmental toxicity was the lowest dose tested (15 mg/kg/day).

In a second juvenile animal study, memantine (0, 1, 3, 8, 15, 30, and 45 mg/kg/day) was orally administered to male and female rats beginning on PND 7 and continuing for various periods during postnatal development. Because of early memantine-related mortality, the 30 and 45 mg/kg/day groups were terminated without further evaluation. Apoptosis or neuronal degeneration in the brain was observed on PNDs 8-17 at a dose of 15 mg/kg/day. The no-effect dose for apoptosis and neuronal degeneration was 8 mg/kg/day. In animals in which memantine (0, 1, 3, 8, or 15 mg/kg/day) was orally administered on PNDs 7-70, adverse neurobehavioral effects (increased locomotor motor activity, increased auditory startle response and decreased habituation, and deficit in learning and memory) were observed at all but the lowest dose tested. Effects on auditory startle persisted after drug discontinuation. The no-effect dose for developmental toxicity was the lowest dose tested (1 mg/kg/day).

8.5 Geriatric Use

The majority of people with Alzheimer’s disease are 65 years of age and older. In the clinical studies of NAMENDA the mean age of patients was approximately 76 years; over 90% of patients were 65 years and older, 60% were 75 years and older, and 12% were at or above 85 years of age. The efficacy and safety data presented in the clinical trial sections were obtained from these patients. There were no clinically meaningful differences in most adverse events reported by patient groups ≥ 65 years old and < 65 years old.

8.6 Renal Impairment

No dosage adjustment is needed in patients with mild or moderate renal impairment. A dosage reduction is recommended in patients with severe renal impairment [see Dosage and Administration (2) and Clinical Pharmacology (12.3)].

8.7 Hepatic Impairment

No dosage adjustment is needed in patients with mild or moderate hepatic impairment. NAMENDA should be administered with caution to patients with severe hepatic impairment [see Dosage and Administration (2) and Clinical Pharmacology (12.3)].

10 OVERDOSAGE

Signs and symptoms most often accompanying memantine overdosage in clinical trials and from worldwide marketing experience, alone or in combination with other drugs and/or alcohol, include agitation, asthenia, bradycardia, confusion, coma, dizziness, ECG changes, increased blood pressure, lethargy, loss of consciousness, psychosis, restlessness, slowed movement, somnolence, stupor, unsteady gait, visual hallucinations, vertigo, vomiting, and weakness. The largest known ingestion of memantine worldwide was 2 grams in a patient who took memantine in conjunction with unspecified antidiabetic medications. This patient experienced coma, diplopia, and agitation, but subsequently recovered. Fatal outcome has been very rarely reported with memantine, and the relationship to memantine was unclear.

Because strategies for the management of overdose are continually evolving, it is advisable to contact a poison control center to determine the latest recommendations for the management of an overdose of any drug. As in any cases of overdose, general supportive measures should be utilized, and treatment should be symptomatic. Elimination of memantine can be enhanced by acidification of urine.

11 DESCRIPTION

NAMENDA (memantine hydrochloride) is an orally active NMDA receptor antagonist. The chemical name for memantine hydrochloride is 1-amino-3,5-dimethyladamantane hydrochloride with the following structural formula:

The molecular formula is C12H21N•HCl and the molecular weight is 215.76. Memantine hydrochloride occurs as a fine white to off-white powder and is soluble in water.

NAMENDA tablets are available for oral administration as capsule-shaped, film-coated tablets containing 5 mg and 10 mg of memantine hydrochloride. NAMENDA tablets also contain the following inactive ingredients: microcrystalline cellulose/colloidal silicon dioxide, talc, croscarmellose sodium, and magnesium stearate. In addition, the following inactive ingredients are also present as components of the film coat: hypromellose, titanium dioxide, polyethylene glycol 400, FD&C yellow #6 and FD&C blue #2 (5 mg tablets), and hypromellose, titanium dioxide, macrogol/polyethylene glycol 400 and iron oxide black (10 mg tablets).

12 CLINICAL PHARMACOLOGY

12.1 Mechanism of Action

Persistent activation of central nervous system N-methyl-D-aspartate (NMDA) receptors by the excitatory amino acid glutamate has been hypothesized to contribute to the symptomatology of Alzheimer’s disease. Memantine is postulated to exert its therapeutic effect through its action as a low to moderate affinity uncompetitive (open-channel) NMDA receptor antagonist which binds preferentially to the NMDA receptor-operated cation channels. There is no evidence that memantine prevents or slows neurodegeneration in patients with Alzheimer’s disease.

12.2 Pharmacodynamics

Memantine showed low to negligible affinity for GABA, benzodiazepine, dopamine, adrenergic, histamine and glycine receptors and for voltage-dependent Ca^2+, Na^+, or K^+ channels. Memantine also showed antagonistic effects at the 5HT3 receptor with a potency similar to that for the NMDA receptor and blocked nicotinic acetylcholine receptors with one-sixth to one-tenth the potency.

In vitro studies have shown that memantine does not affect the reversible inhibition of acetylcholinesterase by donepezil, galantamine, or tacrine.

12.3 Pharmacokinetics

Absorption

Following oral administration memantine is highly absorbed with peak concentrations reached in about 3-7 hours. Memantine has linear pharmacokinetics over the therapeutic dose range. Food has no effect on the absorption of memantine.

Distribution

The mean volume of distribution of memantine is 9-11 L/kg and the plasma protein binding is low (45%).

Metabolism

Memantine undergoes partial hepatic metabolism. The hepatic microsomal CYP450 enzyme system does not play a significant role in the metabolism of memantine.

Elimination

Memantine is excreted predominantly (about 48%) unchanged in urine and has a terminal elimination half-life of about 60-80 hours.

The remainder is converted primarily to three polar metabolites which possess minimal NMDA receptor antagonistic activity: the N-glucuronide conjugate, 6-hydroxy memantine, and 1-nitroso-deaminated memantine. A total of 74% of the administered dose is excreted as the sum of the parent drug and the N-glucuronide conjugate. Renal clearance involves active tubular secretion moderated by pH dependent tubular reabsorption.

Specific Populations

Gender

Following multiple dose administration of NAMENDA 20 mg daily, females had about 45% higher exposure than males, but there was no difference in exposure when body weight was taken into account.

Elderly

The pharmacokinetics of NAMENDA in young and elderly subjects are similar.

Renal Impairment

Memantine pharmacokinetics were evaluated following single oral administration of 20 mg memantine hydrochloride in 8 subjects with mild renal impairment (creatinine clearance, CLcr, > 50 – 80 mL/min), 8 subjects with moderate renal impairment (CLcr 30 – 49 mL/min), 7 subjects with severe renal impairment (CLcr 5 – 29 mL/min) and 8 healthy subjects (CLcr > 80 mL/min) matched as closely as possible by age, weight and gender to the subjects with renal impairment. Mean AUC0-∞ increased by 4%, 60%, and 115% in subjects with mild, moderate, and severe renal impairment, respectively, compared to healthy subjects. The terminal elimination half-life increased by 18%, 41%, and 95% in subjects with mild, moderate, and severe renal impairment, respectively, compared to healthy subjects.

No dosage adjustment is recommended for patients with mild and moderate renal impairment. Dosage should be reduced in patients with severe renal impairment [see Dosage and Administration (2)].

Hepatic Impairment

Memantine pharmacokinetics were evaluated following the administration of single oral doses of 20 mg in 8 subjects with moderate hepatic impairment (Child-Pugh Class B, score 7-9) and 8 subjects who were age-, gender-, and weight-matched to the hepatically-impaired subjects. There was no change in memantine exposure (based on Cmax and AUC) in subjects with moderate hepatic impairment as compared with healthy subjects. However, terminal elimination half-life increased by about 16% in subjects with moderate hepatic impairment as compared with healthy subjects. No dose adjustment is recommended for patients with mild and moderate hepatic impairment. Memantine should be administered with caution to patients with severe hepatic impairment as the pharmacokinetics of memantine have not been evaluated in that population.

Drug-Drug Interactions

Use with Cholinesterase Inhibitors

Coadministration of memantine with the AChE inhibitor donepezil hydrochloride did not affect the pharmacokinetics of either compound. Furthermore, memantine did not affect AChE inhibition by donepezil. In a 24-week controlled clinical study in patients with moderate to severe Alzheimer’s disease, the adverse event profile observed with a combination of NAMENDA and donepezil was similar to that of donepezil alone.

Effect of NAMENDA on the Metabolism of Other Drugs

In vitro studies conducted with marker substrates of CYP450 enzymes (CYP1A2, -2A6, -2C9, -2D6, -2E1, -3A4) showed minimal inhibition of these enzymes by memantine. In addition, in vitro studies indicate that at concentrations exceeding those associated with efficacy, memantine does not induce the cytochrome P450 isozymes CYP1A2, -2C9, -2E1 and -3A4/5. No pharmacokinetic interactions with drugs metabolized by these enzymes are expected.

Pharmacokinetic studies evaluated the potential of memantine for interaction with warfarin, and bupropion. Memantine did not affect the pharmacokinetics of the CYP2B6 substrate bupropion or its metabolite hydroxy-bupropion. Furthermore, memantine did not affect the pharmacokinetics or pharmacodynamics of warfarin as assessed by the prothrombin INR.

Effect of Other Drugs on NAMENDA

Memantine is predominantly renally eliminated, and drugs that are substrates and/or inhibitors of the CYP450 system are not expected to alter the metabolism of memantine.

Drugs Eliminated via Renal Mechanisms

Because memantine is eliminated in part by tubular secretion, coadministration of drugs that use the same renal cationic system, including hydrochlorothiazide (HCTZ), triamterene (TA), metformin, cimetidine, ranitidine, quinidine, and nicotine, could potentially result in altered plasma levels of both agents. However, coadministration of NAMENDA and HCTZ/TA did not affect the bioavailability of either memantine or TA, and the bioavailability of HCTZ decreased by 20%. In addition, coadministration of memantine with the antihyperglycemic drug Glucovance® (glyburide and metformin hydrochloride) did not affect the pharmacokinetics of memantine, metformin and glyburide. Furthermore, memantine did not modify the serum glucose lowering effect of Glucovance®, indicating the absence of a pharmacodynamic interaction.

Drugs Highly Bound to Plasma Proteins

Because the plasma protein binding of memantine is low (45%), an interaction with drugs that are highly bound to plasma proteins, such as warfarin and digoxin, is unlikely.

13 NONCLINICAL TOXICOLOGY

13.1 Carcinogenesis, Mutagenesis, Impairment of Fertility

There was no evidence of carcinogenicity in a 113-week oral study in mice at doses up to 40 mg/kg/day (10 times the maximum recommended human dose [MRHD] on a mg/m^2 basis). There was also no evidence of carcinogenicity in rats orally dosed at up to 40 mg/kg/day for 71 weeks followed by 20 mg/kg/day (20 and 10 times the MRHD on a mg/m^2 basis, respectively) through 128 weeks.

Memantine produced no evidence of genotoxic potential when evaluated in the in vitro S. typhimurium or E. coli reverse mutation assay, an in vitro chromosomal aberration test in human lymphocytes, an in vivo cytogenetics assay for chromosome damage in rats, and the in vivo mouse micronucleus assay. The results were equivocal in an in vitro gene mutation assay using Chinese hamster V79 cells.

No impairment of fertility or reproductive performance was seen in rats administered up to 18 mg/kg/day (9 times the MRHD on a mg/m^2 basis) orally from 14 days prior to mating through gestation and lactation in females, or for 60 days prior to mating in males.

13.2 Animal Toxicology and/or Pharmacology

Memantine induced neuronal lesions (vacuolation and necrosis) in the multipolar and pyramidal cells in cortical layers III and IV of the posterior cingulate and retrosplenial neocortices in rats, similar to those which are known to occur in rodents administered other NMDA receptor antagonists. Lesions were seen after a single dose of memantine. In a study in which rats were given daily oral doses of memantine for 14 days, the no-effect dose for neuronal necrosis was 6 times the maximum recommended human dose of 20 mg/day on a mg/m^2 basis.

In acute and repeat-dose neurotoxicity studies in female rats, oral administration of memantine and donepezil in combination resulted in increased incidence, severity, and distribution of neurodegeneration compared with memantine alone. The no-effect levels of the combination were associated with clinically relevant plasma memantine and donepezil exposures.

The relevance of these findings to humans is unknown.

14 CLINICAL STUDIES

The effectiveness of NAMENDA as a treatment for patients with moderate to severe Alzheimer’s disease was demonstrated in 2 randomized, double-blind, placebo-controlled clinical studies (Studies 1 and 2) conducted in the United States that assessed both cognitive function and day to day function. The mean age of patients participating in these two trials was 76 years with a range of 50-93 years. Approximately 66% of patients were female and 91% of patients were Caucasian. A third study (Study 3), carried out in Latvia, enrolled patients with severe dementia, but did not assess cognitive function as a planned endpoint. Study Outcome Measures: In each U.S. study, the effectiveness of NAMENDA was determined using both an instrument designed to evaluate overall function through caregiver-related assessment, and an instrument that measures cognition. Both studies showed that patients on NAMENDA experienced significant improvement on both measures compared to placebo.

Day-to-day function was assessed in both studies using the modified Alzheimer’s disease Cooperative Study - Activities of Daily Living inventory (ADCS-ADL). The ADCS-ADL consists of a comprehensive battery of ADL questions used to measure the functional capabilities of patients. Each ADL item is rated from the highest level of independent performance to complete loss. The investigator performs the inventory by interviewing a caregiver familiar with the behavior of the patient. A subset of 19 items, including ratings of the patient’s ability to eat, dress, bathe, telephone, travel, shop, and perform other household chores has been validated for the assessment of patients with moderate to severe dementia. This is the modified ADCS-ADL, which has a scoring range of 0 to 54, with the lower scores indicating greater functional impairment.

The ability of NAMENDA to improve cognitive performance was assessed in both studies with the Severe Impairment Battery (SIB), a multi-item instrument that has been validated for the evaluation of cognitive function in patients with moderate to severe dementia. The SIB examines selected aspects of cognitive performance, including elements of attention, orientation, language, memory, visuospatial ability, construction, praxis, and social interaction. The SIB scoring range is from 0 to 100, with lower scores indicating greater cognitive impairment.

Study 1 (Twenty-Eight-Week Study)

In a study of 28 weeks duration, 252 patients with moderate to severe probable Alzheimer’s disease (diagnosed by DSM-IV and NINCDS-ADRDA criteria, with Mini-Mental State Examination scores ≥ 3 and ≤ 14 and Global Deterioration Scale Stages 5-6) were randomized to NAMENDA or placebo. For patients randomized to NAMENDA, treatment was initiated at 5 mg once daily and increased weekly by 5 mg/day in divided doses to a dose of 20 mg/day (10 mg twice a day).

Effects on the ADCS-ADL

Figure 1 shows the time course for the change from baseline in the ADCS-ADL score for patients in the two treatment groups completing the 28 weeks of the study. At 28 weeks of treatment, the mean difference in the ADCS-ADL change scores for the NAMENDA-treated patients compared to the patients on placebo was 3.4 units. Using an analysis based on all patients and carrying their last study observation forward (LOCF analysis), NAMENDA treatment was statistically significantly superior to placebo.

Figure 1: Time course of the change from baseline in
ADCS-ADL score for patients completing 28 weeks of treatment

Figure 2 shows the cumulative percentages of patients from each of the treatment groups who had attained at least the change in the ADCS-ADL shown on the X axis. The curves show that both patients assigned to NAMENDA and placebo have a wide range of responses and generally show deterioration (a negative change in ADCS-ADL compared to baseline), but that the NAMENDA group is more likely to show a smaller decline or an improvement. (In a cumulative distribution display, a curve for an effective treatment would be shifted to the left of the curve for placebo, while an ineffective or deleterious treatment would be superimposed upon or shifted to the right of the curve for placebo).

Figure 2: Cumulative percentage of patients completing 28 weeks of

double-blind treatment with specified changes from baseline in ADCS-ADL scores

Effects on the SIB

Figure 3 shows the time course for the change from baseline in SIB score for the two treatment groups over the 28 weeks of the study. At 28 weeks of treatment, the mean difference in the SIB change scores for the NAMENDA-treated patients compared to the patients on placebo was 5.7 units. Using an LOCF analysis, NAMENDA treatment was statistically significantly superior to placebo.

Figure 3: Time course of the change from baseline in

SIB score for patients completing 28 weeks of treatment

Figure 4 shows the cumulative percentages of patients from each treatment group who had attained at least the measure of change in SIB score shown on the X axis. The curves show that both patients assigned to NAMENDA and placebo have a wide range of responses and generally show deterioration, but that the NAMENDA group is more likely to show a smaller decline or an improvement.

Figure 4: Cumulative percentage of patients completing 28 weeks of

double-blind treatment with specified changes from baseline in SIB scores

Study 2 (Twenty-Four-Week Study)

In a study of 24 weeks duration, 404 patients with moderate to severe probable Alzheimer’s disease (diagnosed by NINCDS-ADRDA criteria, with Mini-Mental State Examination scores ≥ 5 and ≤ 14) who had been treated with donepezil for at least 6 months and who had been on a stable dose of donepezil for the last 3 months were randomized to NAMENDA or placebo while still receiving donepezil. For patients randomized to NAMENDA, treatment was initiated at 5 mg once daily and increased weekly by 5 mg/day in divided doses to a dose of 20 mg/day (10 mg twice a day).

Effects on the ADCS-ADL

Figure 5 shows the time course for the change from baseline in the ADCS-ADL score for the two treatment groups over the 24 weeks of the study. At 24 weeks of treatment, the mean difference in the ADCS-ADL change scores for the NAMENDA/donepezil treated patients (combination therapy) compared to the patients on placebo/donepezil (monotherapy) was 1.6 units. Using an LOCF analysis, NAMENDA/donepezil treatment was statistically significantly superior to placebo/donepezil.

Figure 5: Time course of the change from baseline in

ADCS-ADL score for patients completing 24 weeks of treatment

Figure 6 shows the cumulative percentages of patients from each of the treatment groups who had attained at least the measure of improvement in the ADCS-ADL shown on the X axis. The curves show that both patients assigned to NAMENDA/donepezil and placebo/donepezil have a wide range of responses and generally show deterioration, but that the NAMENDA/donepezil group is more likely to show a smaller decline or an improvement.

Figure 6: Cumulative percentage of patients completing 24 weeks of

double-blind treatment with specified changes from baseline in ADCS-ADL scores

Effects on the SIB

Figure 7 shows the time course for the change from baseline in SIB score for the two treatment groups over the 24 weeks of the study. At 24 weeks of treatment, the mean difference in the SIB change scores for the NAMENDA/donepezil-treated patients compared to the patients on placebo/donepezil was 3.3 units. Using an LOCF analysis, NAMENDA/donepezil treatment was statistically significantly superior to placebo/donepezil.

Figure 7: Time course of the change from baseline in

SIB score for patients completing 24 weeks of treatment

Figure 8 shows the cumulative percentages of patients from each treatment group who had attained at least the measure of improvement in SIB score shown on the X axis. The curves show that both patients assigned to NAMENDA/donepezil and placebo/donepezil have a wide range of responses, but that the NAMENDA/donepezil group is more likely to show an improvement or a smaller decline.

Figure 8: Cumulative percentage of patients completing 24 weeks of

double-blind treatment with specified changes from baseline in SIB scores

Study 3 (Twelve-Week Study)

In a double-blind study of 12 weeks duration, conducted in nursing homes in Latvia, 166 patients with dementia according to DSM-III-R, a Mini-Mental State Examination score of < 10, and Global Deterioration Scale staging of 5 to 7 were randomized to either NAMENDA or placebo. For patients randomized to NAMENDA, treatment was initiated at 5 mg once daily and increased to 10 mg once daily after 1 week. The primary efficacy measures were the care dependency subscale of the Behavioral Rating Scale for Geriatric Patients (BGP), a measure of day-to-day function, and a Clinical Global Impression of Change (CGI-C), a measure of overall clinical effect. No valid measure of cognitive function was used in this study. A statistically significant treatment difference at 12 weeks that favored NAMENDA over placebo was seen on both primary efficacy measures. Because the patients entered were a mixture of Alzheimer’s disease and vascular dementia, an attempt was made to distinguish the two groups and all patients were later designated as having either vascular dementia or Alzheimer’s disease, based on their scores on the Hachinski Ischemic Scale at study entry. Only about 50% of the patients had computerized tomography of the brain. For the subset designated as having Alzheimer’s disease, a statistically significant treatment effect favoring NAMENDA over placebo at 12 weeks was seen on both the BGP and CGI-C.

16 HOW SUPPLIED/STORAGE AND HANDLING

5 mg Tablets:

Tan, capsule-shaped, film-coated tablets with “5” debossed on one side and “FL” on the other side.

Bottle of 60 NDC #0456-3205-60

10 x 10 Unit Dose NDC #0456-3205-63

10 mg Tablets:

Gray, capsule-shaped, film-coated tablets with “10” debossed on one side and “FL” on the other side.

Bottle of 60 NDC #0456-3210-60

10 x 10 Unit Dose NDC #0456-3210-63

Titration Pack: NDC #0456-3200-14

Blister package containing 49 tablets (28 x 5 mg and 21 x 10 mg tablets).

Store NAMENDA Tablets at 25°C (77°F); excursions permitted to 15-30°C (59-86°F) [see USP Controlled Room Temperature].

17 PATIENT COUNSELING INFORMATION

Advise the patient to read the FDA-approved patient labeling (Patient Information).

To assure safe and effective use of NAMENDA, the following information and instructions provided in the patient information section should be discussed with patients and caregivers.

Patients/caregivers should be instructed to follow the dose titration schedule provided by their physician or healthcare professional for NAMENDA. They should be warned not to use any tablets of NAMENDA that are damaged or show signs of tampering.

If a patient misses a single dose of NAMENDA, that patient should not double up on the next dose. The next dose should be taken as scheduled. If a patient fails to take NAMENDA for several days, dosing should not be resumed without consulting that patient’s healthcare professional.

Made in Ireland

Distributed by:
Allergan USA, Inc.
Madison, NJ 07940

Licensed from Merz Pharmaceuticals GmbH

NAMENDA® is a registered trademark of Merz Pharma GmbH & Co KGaA

All other trademarks are the property of their respective owners.

Allergan® and its design are trademarks of Allergan, Inc.

© 2019 Allergan. All rights reserved.
v1.1USPI3205

Patient Information

NAMENDA® [Nuh-MEN-dah]

(memantine hydrochloride)

Tablets

Read this Patient Information that comes with NAMENDA before you start taking it and each time you get a refill. There may be new information. This information does not take the place of talking to your doctor about your medical condition or your treatment.

What is NAMENDA?

NAMENDA® is a prescription medicine used for the treatment of moderate to severe dementia in people with Alzheimer’s disease. NAMENDA belongs to a class of medicines called N-methyl-D-aspartate (NMDA) inhibitors.

It is not known if NAMENDA is safe and effective in children.

Who should not take NAMENDA?

Do not take NAMENDA if you are allergic to memantine or any of the ingredients in NAMENDA tablets. See the end of this leaflet for a complete list of ingredients in NAMENDA tablets.

What should I tell my doctor before taking NAMENDA?

Before you take NAMENDA, tell your doctor if you:

- have or have had seizures
- have or have had problems passing urine
- have or have had bladder or kidney problems
- have liver problems
- have any other medical conditions
- are pregnant or plan to become pregnant. It is not known if NAMENDA will harm your unborn baby.
- are breastfeeding or plan to breastfeed. It is not known if memantine passes into your breast milk. Talk to your doctor about the best way to feed your baby if you take NAMENDA.

Tell your doctor about all the medicines you take, including prescription and non-prescription medicines, vitamins, and herbal supplements.

Taking NAMENDA with certain other medicines may affect each other. Taking NAMENDA with other medicines can cause serious side effects.

Especially tell your doctor if you take:

- other NMDA antagonists such as amantadine, ketamine, and dextromethorphan
- medicines that make your urine alkaline such as carbonic anhydrase inhibitors and sodium bicarbonate

Ask your doctor or pharmacist for a list of these medicines, if you are not sure.

Know the medicines you take. Keep a list of them to show your doctor and pharmacist when you get a new medicine.

How should I take NAMENDA?

- Your doctor will tell you how much NAMENDA to take and when to take it.
- Your doctor may change your dose if needed.
- NAMENDA can be taken with food or without food.
- Do not use any tablets of NAMENDA that are damaged or show signs of tampering.
- If you forget to take one dose of NAMENDA, do not double up on the next dose. You should take only the next dose as scheduled.
- If you have forgotten to take NAMENDA for several days, you should not take the next dose until you talk to your doctor.
- If you take too much NAMENDA, call your doctor or poison control center at 1-800-222-1222, or go to the nearest hospital emergency room right away.

What are the possible side effects of NAMENDA?

NAMENDA may cause side effects, including:

The most common side effects of NAMENDA include:

- dizziness
- headache
- confusion
- constipation

These are not all the possible side effects of NAMENDA. For more information, ask your doctor or pharmacist.

Call your doctor for medical advice about side effects. You may report side effects to FDA at 1-800-FDA-1088.

How should I store NAMENDA?

- Store NAMENDA at room temperature between 68°F to 77°F (20°C to 25°C).

What are the ingredients in NAMENDA?

NAMENDA tablets:

Active ingredient: memantine hydrochloride

Inactive ingredients: microcrystalline cellulose/colloidal silicon dioxide, talc, croscarmellose sodium, and magnesium stearate

Inactive ingredients of tablet film coating: hypromellose, titanium dioxide, polyethylene glycol 400, FD&C yellow #6 and FD&C blue #2 (5 mg tablets), and hypromellose, titanium dioxide, macrogol/polyethylene glycol 400 and iron oxide black (10 mg tablets)

Keep NAMENDA and all medicines out of the reach of children.

General information about the safe and effective use of NAMENDA.

Medicines are sometimes prescribed for purposes other than those listed in a Patient Information leaflet. Do not take NAMENDA for a condition for which it was not prescribed. Do not give NAMENDA to other people, even if they have the same condition. It may harm them.

This Patient Information leaflet summarizes the most important information about NAMENDA. If you would like more information, talk with your doctor. You can ask your doctor or pharmacist for information about NAMENDA that was written for healthcare professionals.

For more information about NAMENDA, go to www.namenda.com, or call Allergan at 1-800-678-1605.

This Patient Information has been approved by the U.S. Food and Drug Administration.

Made in Ireland

Distributed by:
Allergan USA, Inc.
Madison, NJ 07940

Licensed from Merz Pharmaceuticals GmbH

NAMENDA® is a registered trademark of Merz Pharma GmbH & Co KGaA

Allergan® and its design are trademarks of Allergan, Inc.

© 2019 Allergan. All rights reserved.

Content updated: November 2018

v1.1PPI3205

PRINCIPAL DISPLAY PANEL

Rx Only NDC 0456-3205-60
Namenda
memantine HCl tablets
5 mg
60 Tablets

PRINCIPAL DISPLAY PANEL

Rx Only NDC 0456-3210-60
Namenda
memantine HCl tablets
10 mg
60 Tablets

PRINCIPAL DISPLAY PANEL

Rx Only NDC 0456-3200-14
Namenda
memantine HCl tablets
TITRATION PAK